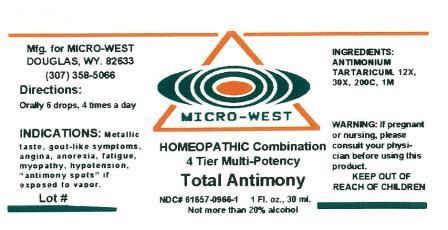 DRUG LABEL: Total Antimony
                
NDC: 61657-0966 | Form: LIQUID
Manufacturer: White Manufacturing Inc. DBA Micro -West
Category: homeopathic | Type: HUMAN OTC DRUG LABEL
Date: 20160420

ACTIVE INGREDIENTS: ANTIMONY POTASSIUM TARTRATE 12 [hp_X]/30 mL
INACTIVE INGREDIENTS: Alcohol

Drug Facts

Active Ingredients

antimonium tartaricum 12x,30x,200c,1m

Uses

Metallic taste, gout-like symptoms, angina, anorexia, fatigue, myopathy, hypotension,

Keep Out of Reach of Children

INDICATIONS

INDICATIONS: Metallic taste, gout-like symptoms, angina, anorexia, fatigue, myopathy, hypotension, "antimony spots" if exposed to vapor

Ask Doctor

If pregnant or nursing, please consult physician before using this product

Directions

Directions: Orally 6 drops, 4 times a day

Inactive Ingredient

Not more than 20% Alcohol

Manufactured for Micro West

Douglas, WY 82633

1-307-358-5066